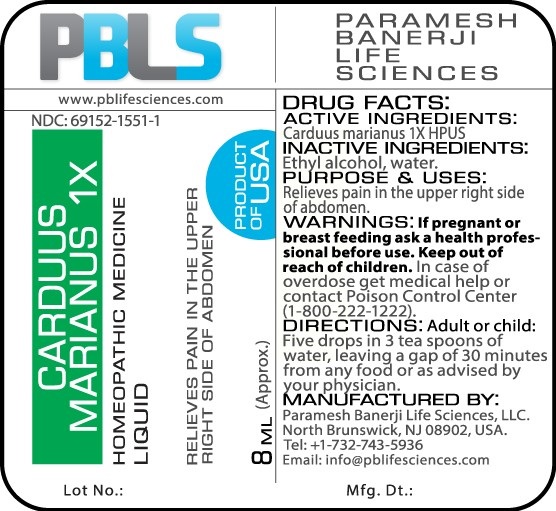 DRUG LABEL: Carduus marianus 1X
NDC: 69152-1551 | Form: LIQUID
Manufacturer: Paramesh Banerji Life Sciences LLC
Category: homeopathic | Type: HUMAN OTC DRUG LABEL
Date: 20170310

ACTIVE INGREDIENTS: MILK THISTLE 1 [hp_X]/8 mL
INACTIVE INGREDIENTS: ALCOHOL; WATER

DRUG FACTS: Active Ingredient

Carduus marianus 1X HPUS

Inactive Ingredients

Ethyl alcohol, Water

Purpose

Relieves pain in the upper right side of abdomen

Uses

Relieves pain in the upper right side of abdomen

Warnings

If pregnant or breast feeding ask a health professional before use.

Keep out of reach of children. In case of overdose, get medical help or contact a Poison Control Center (1-800-222-1222) right away.

Direction

Adult or child: Five drops in 3 tea spoons of water, leaving a gap of 30 minutes from any food or as advised by your physician.

Manufactured by

Paramesh Banerji Life Sciences, LLC.

North Brunswick, NJ 08902, USA.

Tel: +1-732-743-5936

Email: info@pblifesciences.com

Principal Display Panel

NDC: 69152-1551-1

Carduus marianus 1X

Homeopathic Medicine

Liquid

Relieves pain in the upper right side of abdomen

8 mL (Approx.)

Product of USA